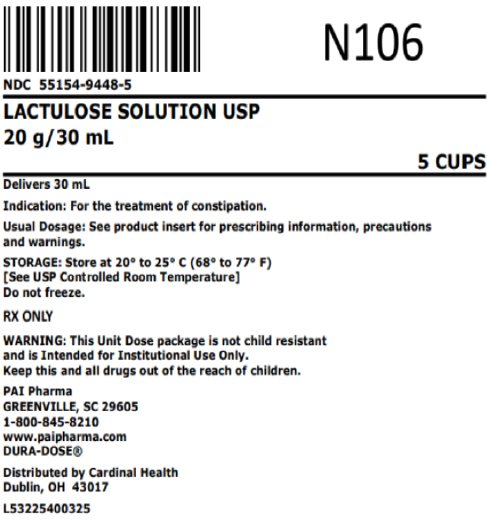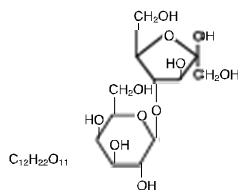 DRUG LABEL: LACTULOSE
NDC: 55154-9448 | Form: SOLUTION
Manufacturer: Cardinal Health 107, LLC
Category: prescription | Type: HUMAN PRESCRIPTION DRUG LABEL
Date: 20260114

ACTIVE INGREDIENTS: LACTULOSE 20 g/30 mL
INACTIVE INGREDIENTS: FD&C YELLOW NO. 6; WATER; SODIUM HYDROXIDE

Lactulose Solution USP 10 g/15 mL

I05770918
R09/18

Rx ONLY

DESCRIPTION

Lactulose is a synthetic disaccharide in solution form for oral administration. Each 15 mL of Lactulose Solution contains: 10 g lactulose (and less than 1.6 g galactose, less than 1.2 g lactose, and 1.2 g or less of other sugars). Also contains FD&C Yellow No. 6, purified water, and flavoring. Sodium hydroxide used to adjust pH. The pH range is 2.5 to 6.5.

Lactulose is a colonic acidifier which promotes laxation.

The chemical name for lactulose is 4-0-ß-D-galactopyranosyl-D-fructofuranose. It has the following structural formula:

The molecular weight is 342.30. It is freely soluble in water.

CLINICAL PHARMACOLOGY

Lactulose is poorly absorbed from the gastrointestinal tract, and no enzyme capable of hydrolysis of this disaccharide is present in human gastrointestinal tissue. As a result, oral doses of lactulose solution reach the colon virtually unchanged. In the colon, lactulose is broken down primarily to lactic acid, and also to small amounts of formic and acetic acids, by the action of colonic bacteria, which results in an increase in osmotic pressure and slight acidification of the colonic contents. This in turn causes an increase in stool water content and softens the stool.

Since lactulose does not exert its effect until it reaches the colon, and since transit time through the colon may be slow, 24 to 48 hours may be required to produce the desired bowel movement.

Lactulose solution given orally to man and experimental animals resulted in only small amounts reaching the blood.

Urinary excretion has been determined to be 3% or less and is essentially complete within 24 hours.

INDICATIONS AND USAGE

For the treatment of constipation. In patients with a history of chronic constipation, lactulose solution therapy increases the number of bowel movements per day and the number of days on which bowel movements occur.

CONTRAINDICATIONS

Since lactulose solution contains galactose (less than 1.6 g/15 mL), it is contraindicated in patients who require a low galactose diet.

WARNINGS

A theoretical hazard may exist for patients being treated with lactulose solution who may be required to undergo electrocautery procedures during proctoscopy or colonoscopy. Accumulation of H2 gas in significant concentration in the presence of an electrical spark may result in an explosive reaction. Although this complication has not been reported with lactulose, patients on lactulose therapy undergoing such procedures should have a thorough bowel cleansing with a non-fermentable solution. Insufflation of CO2 as an additional safeguard may be pursued but is considered to be a redundant measure.

PRECAUTIONS

General

Since lactulose solution contains galactose (less than1.6 g/15 mL) and lactose (less than 1.2 g/15 mL), it should be used with caution in diabetics.

Information for Patients

In the event that an unusual diarrheal condition occurs, contact your physician.

Laboratory Tests

Elderly, debilitated patients who receive lactulose solution for more than six months should have serum electrolytes (potassium, chloride, carbon dioxide) measured periodically.

Drug Interactions

Results of preliminary studies in humans and rats suggest that nonabsorbable antacids given concurrently with lactulose may inhibit the desired lactulose-induced drop in colonic pH. Therefore, a possible lack of desired effect of treatment should be taken into consideration before such drugs are given concomitantly with lactulose solution.

Carcinogenesis, Mutagenesis, Impairment of Fertility

There are no known human data on long-term potential for carcinogenicity, mutagenicity, or impairment of fertility.

There are no known animal data on long-term potential for mutagenicity.

Administration of lactulose solution in the diet of mice for 18 months in concentrations of 3 and 10 percent (V/W) did not produce any evidence of carcinogenicity.

In studies in mice, rats, and rabbits, doses of lactulose solution up to 6 or 12 mL/kg/day produced no deleterious effects in breeding, conception, or parturition.

Pregnancy:Teratogenic Effects.

Pregnancy Category B: Reproduction studies have been performed in mice, rats, and rabbits at doses up to 3 or 6 times the usual human oral dose and have revealed no evidence of impaired fertility or harm to the fetus due to lactulose. There are, however, no adequate and well-controlled studies in pregnant women. Because animal reproduction studies are not always predictive of human response, this drug should be used during pregnancy only if clearly needed.

Nursing Mothers

It is not known whether this drug is excreted in human milk. Because many drugs are excreted in human milk, caution should be exercised when lactulose solution is administered to a nursing woman.

Pediatric Use

Safety and effectiveness in pediatric patients have not been established.

ADVERSE REACTIONS

Precise frequency data are not available.

Initial dosing may produce flatulence and intestinal cramps, which are usually transient. Excessive dosage can lead to diarrhea with potential complications such as loss of fluids, hypokalemia, and hypernatremia.

Nausea and vomiting have been reported.

To report SUSPECTED ADVERSE REACTIONS, contact Pharmaceutical Associates, Inc. at 1-800-845-8210.

OVERDOSAGE

Signs and Symptoms

There have been no reports of accidental overdosage. In the event of overdosage, it is expected that diarrhea and abdominal cramps would be the major symptoms. Medication should be terminated.

Oral LD50

The acute oral LD50 of the drug is 48.8 mL/kg in mice and greater than 30 mL/kg in rats.

Dialysis

Dialysis data are not available for lactulose. Its molecular similarity to sucrose, however, would suggest that it should be dialyzable.

DOSAGE AND ADMINISTRATION

The usual dose is 1 to 2 tablespoonfuls (15 to 30 mL, containing 10 g to 20 g of lactulose) daily. The dose may be increased to 60 mL daily if necessary. Twenty-four to 48 hours may be required to produce a normal bowel movement.

Note: Some patients have found that lactulose solution may be more acceptable when mixed with fruit juice, water or milk.

HOW SUPPLIED

Overbagged with 5 x 30 mL unit dose cups in each bag, NDC 55154-9448-5

WARNING: This Unit Dose package is not child resistant and is Intended for Institutional Use Only. Keep this and all drugs out of the reach of children.

Lactulose solution contains lactulose 667 mg/mL (10 g/15 mL).

STORAGE AND HANDLING

Store at controlled room temperature, 20°-25°C (68°-77°F). [See USP] Do not freeze.

Under recommended storage conditions, a normal darkening of color may occur. Such darkening is characteristic of sugar solutions and does not affect therapeutic action. Prolonged exposure to temperatures above 30°C (86°F) or to direct light may cause extreme darkening and turbidity which may be pharmaceutically objectionable. If this condition develops, do not use.

Prolonged exposure to freezing temperatures may cause change to a semisolid, too viscous to pour. Viscosity will return to normal upon warming to room temperature.

Keep tightly closed.

Dispense in original container or tight, light-resistant container with a child-resistant closure.

To the Pharmacist: When ordering this product, include the product number (or NDC) in the description.

MANUFACTURED BY

pai
Pharmaceutical
Associates, Inc.
Greenville, SC 29605

Distributed By:

Cardinal Health

Dublin, OH 43017

L53225400325

R09/18

Package/Label Display Panel

NDC 55154-9448-5

LACTULOSE SOLUTION USP

20 g/30 mL

5 CUPS